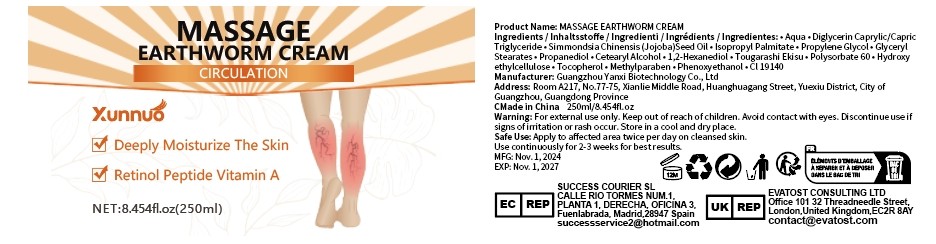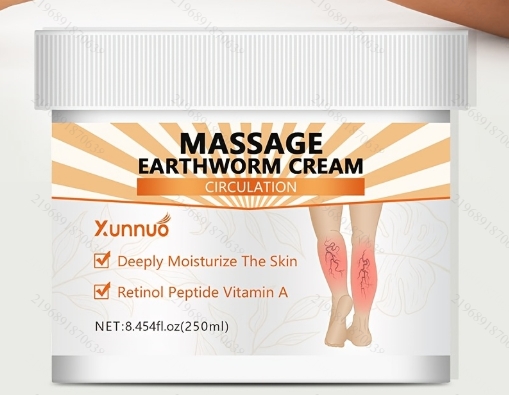 DRUG LABEL: Massage Eaethworm Cream
NDC: 84025-298 | Form: CREAM
Manufacturer: Guangzhou Yanxi Biotechnology Co., Ltd
Category: otc | Type: HUMAN OTC DRUG LABEL
Date: 20241226

ACTIVE INGREDIENTS: TOCOPHEROL 5 mg/100 mL
INACTIVE INGREDIENTS: WATER

DOSAGE AND ADMINISTRATION

Apply to affected area twice per day on cleansed skin.Use continuouslyfor 2-3 weeks for bestresults

WARNINGS

keep out of children

INACTIVE INGREDIENT

Aqua

INDICATIONS AND USAGE

for skin clean

keep out of children

PURPOSE

Deeply Moisturize The Skin